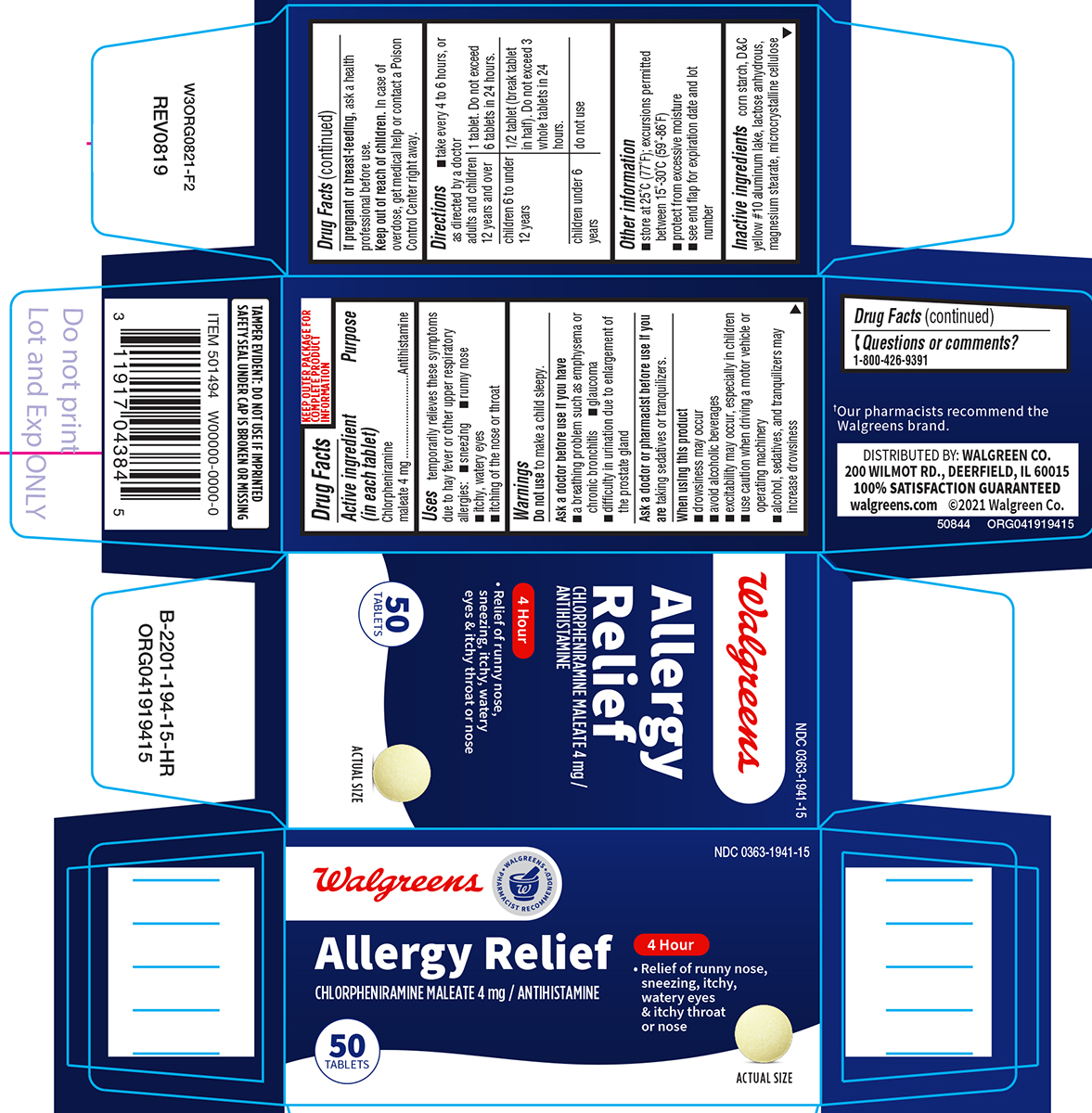 DRUG LABEL: Allergy Relief
NDC: 0363-1941 | Form: TABLET
Manufacturer: Walgreen Company
Category: otc | Type: HUMAN OTC DRUG LABEL
Date: 20250904

ACTIVE INGREDIENTS: CHLORPHENIRAMINE MALEATE 4 mg/1 1
INACTIVE INGREDIENTS: STARCH, CORN; D&C YELLOW NO. 10 ALUMINUM LAKE; ANHYDROUS LACTOSE; MAGNESIUM STEARATE; MICROCRYSTALLINE CELLULOSE

Walgreens 44-194-Allergy

Active ingredient (in each tablet)

Chlorpheniramine maleate 4 mg

Purpose

Antihistamine

Uses

temporarily relieves these symptoms due to hay fever or other upper respiratory allergies:

- sneezing
- runny nose
- itchy, watery eyes
- itching of the nose or throat

Warnings

Do not use

to make a child sleepy.

Ask a doctor before use if you have

- a breathing problem such as emphysema or chronic bronchitis
- glaucoma
- difficulty in urination due to enlargement of the prostate gland

Ask a doctor or pharmacist before use if you are

taking sedatives or tranquilizers.

When using this product

- drowsiness may occur
- avoid alcoholic beverages
- excitability may occur, especially in children
- use caution when driving a motor vehicle or operating machinery
- alcohol, sedatives, and tranquilizers may increase drowsiness

If pregnant or breast-feeding,

ask a health professional before use.

Keep out of reach of children.

In case of overdose, get medical help or contact a Poison Control Center right away.

Directions

- take every 4 to 6 hours, or as directed by a doctor

adults and children 12 years and over | 1 tablet. Do not exceed 6 tablets in 24 hours.
children 6 to under 12 years | 1/2 tablet (break tablet in half). Do not exceed 3 whole tablets in 24 hours.
children under 6 years | do not use

Other information

- store at 25°C (77°F); excursions permitted between 15°-30°C (59°-86°F)
- protect from excessive moisture
- see end flap for expiration date and lot number

Inactive ingredients

corn starch, D&C yellow #10 aluminum lake, lactose anhydrous, magnesium stearate, microcrystalline cellulose

Questions or comments?

1-800-426-9391

Principal display panel

Walgreens

• WALGREENS •
PHARMACIST RECOMMENDED†

NDC 0363-1941-15

Allergy Relief

CHLORPHENIRAMINE MALEATE 4 mg / ANTIHISTAMINE

4 HOUR

• Relief of runny nose,
sneezing, itchy,
watery eyes
& itchy throat
or nose

50
TABLETS

ACTUAL SIZE

TAMPER EVIDENT: DO NOT USE IF IMPRINTED
SAFETY SEAL UNDER CAP IS BROKEN OR MISSING

†Our pharmacists recommend the
Walgreens brand

DISTRIBUTED BY: WALGREEN CO.
200 WILMOT RD., DEERFIELD, IL 60015
100% SATISFACTION GUARANTEED
walgreens.com ©2021 Walgreen Co.

50844 ORG041919415

Walgreens 44-194